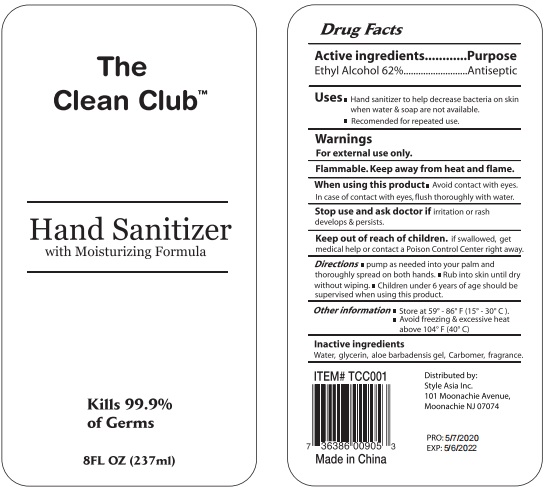 DRUG LABEL: The Clean Club Hand Sanitizer with Moisturizing Formula
NDC: 75780-016 | Form: GEL
Manufacturer: NINGBO MEINEKE Biotech Technology Co., Ltd.
Category: otc | Type: HUMAN OTC DRUG LABEL
Date: 20200522

ACTIVE INGREDIENTS: alcohol 62 mL/100 mL
INACTIVE INGREDIENTS: WATER; PROPYLENE GLYCOL; ALOE VERA LEAF; CARBOMER 934; GLYCERIN; TROLAMINE

Drug facts

Active ingredient(s) Purpose

Ethyl Alcohol 62% ............... Antiseptic

PURPOSE

- Hand sanitizer to help decrease bacteria on the skin.
- When water, soap and towel are not available.
- Recommendd for repeated use.

KEEP OUT OF REACH OF CHILDREN

if swallowed, get medical help or contact a Poison Control Center right away.

INDICATIONS AND USAGE

- pump as needed into your palm and thotoughly spread on both hands.
- Rub into skin until dry without wiping.
- Children under 6 years of age should be supervised when using this product.

WARNINGS

For external use only.
Flammable. Keep away from heat or flame.

Do not apply around eyes. Do not use in ears and mouth.

When using this product, avoid contact with eyes. In case of contact, flush eyes thoroughly with water.

Stop using, consult doctor if irritation or rash develop and persist.

Other information:

- Store at 59-86℉(15-30℃)
- Avoid freezing and excsive heat above 104℉（40℃）

INACTIVE INGREDIENT

Water, Glycerin, Aloe Barbadensis gel, carbomer, fragrance